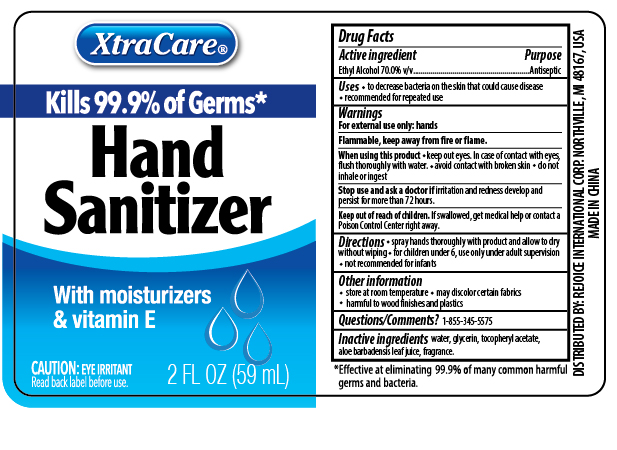 DRUG LABEL: Hand Sanitizer 1.8 oz Antiseptic
NDC: 57337-107 | Form: LIQUID
Manufacturer: REJOICE INTERNATIONAL CORP.
Category: otc | Type: HUMAN OTC DRUG LABEL
Date: 20250206

ACTIVE INGREDIENTS: ALCOHOL 70 mL/100 mL
INACTIVE INGREDIENTS: GLYCERIN; WATER; ALPHA-TOCOPHEROL ACETATE; ALOE VERA LEAF

Hand Sanitizer Spray 1.8oz Antiseptic

ACTIVE INGREDIENT

Ethyl Alcohol 70.0% v/v

PURPOSE

Anitseptic

INDICATIONS AND USAGE

- to decrease bacteria on the skin that could cause disease
- recommended for repeated use

WARNINGS

For external use only: hands

Flammable, keep away from fire or flame

WHEN USING

- keep out eyes. In case of contact with eyes, flush thoroughly with water
- avoid contact with broken skin
- do not inhale or ingest

Stop use and ask a doctor if irritation and redness develop and persist for more than 72 hours.

Keep out of reach of children. If swallowed, get medical help or contact a Poison Control Center right away.

DOSAGE AND ADMINISTRATION

- spray hand thoroughly with product and allow to dry without wiping
- for children under 6, use only under adult supervision
- not recommended for infants

OTHER SAFETY INFORMATION

- store at room temperature
- may discolor certain fabrics
- harmful to wood finished and plastics

INACTIVE INGREDIENT

water, glycerin, tocopheryl acetate, aloe barbadensis leaf juice, fragrance.